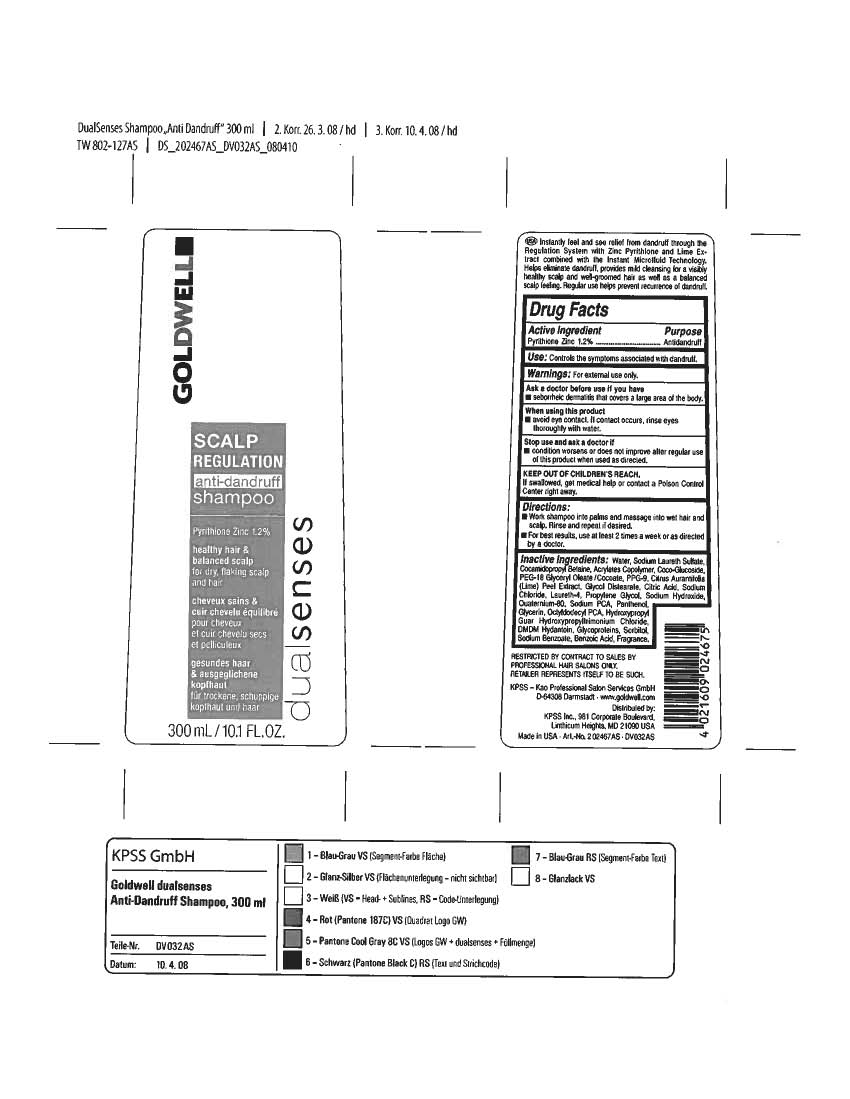 DRUG LABEL: Dual Senses Scalp Regulation AntiDandruff Shampoo
NDC: 25237-0517 | Form: SHAMPOO
Manufacturer: KPSS Inc.
Category: otc | Type: HUMAN OTC DRUG LABEL
Date: 20100101

ACTIVE INGREDIENTS: Pyrithione Zinc 1.2 g/100 g

Drug Facts

Active Ingredient: Pyrithione Zinc 1.2%

Purpose: Antidandruff

INDICATIONS AND USAGE

Use: Controls the symptoms associated with dandruff.

Warnings: For external use only.

Ask a doctor before use if you have: seborreic dermatitis that covers a large area of the body.

When using this product: avoid eye contact. If contact occurs, rinse eyes thoroughly with water.

Stop use and ask a doctor if: condition worsens or does not improve after regular use of this product when used as directed.

KEEP OUT OF REACH OF CHILDREN

Keep Out of Children's Reach: If swallowed, get medical help or contact a Poison Control Center right away.

INDICATIONS AND USAGE

Directions: Work shampoo into palms and massage into wet hair and scalp. Rinse and repeat if desired. For best results, use at least 2 times a week or as directed by a doctor.

QUESTIONS

Distributed by KPSS Inc., 981 Corporate Boulevard, Linthicum Heights, MD 21090 USA

PACKAGE LABEL

MM1: 10oz_DSSR_antidandruff_shampoo_label.jpg